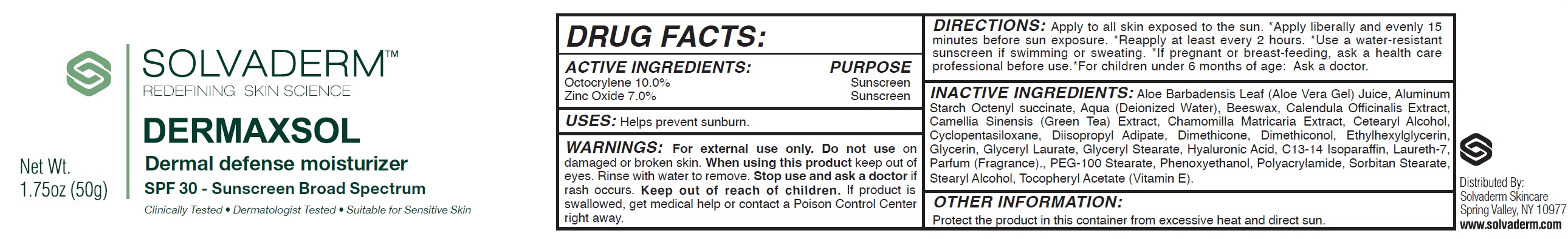 DRUG LABEL: SOLVADERM Dermaxsol Dermal Defense Moisturizer SPF-30
NDC: 84197-467 | Form: CREAM
Manufacturer: SOLVADERM LLC
Category: otc | Type: HUMAN OTC DRUG LABEL
Date: 20240321

ACTIVE INGREDIENTS: OCTOCRYLENE 100 mg/1 g; ZINC OXIDE 70 mg/1 g
INACTIVE INGREDIENTS: ALOE VERA LEAF; ALUMINUM STARCH OCTENYLSUCCINATE; WATER; YELLOW WAX; CALENDULA OFFICINALIS FLOWER; GREEN TEA LEAF; CETOSTEARYL ALCOHOL; CYCLOMETHICONE 5; DIISOPROPYL ADIPATE; DIMETHICONE; ETHYLHEXYLGLYCERIN; GLYCERIN; GLYCERYL LAURATE; GLYCERYL MONOSTEARATE; HYALURONIC ACID; C13-14 ISOPARAFFIN; LAURETH-7; PEG-100 STEARATE; PHENOXYETHANOL; SORBITAN MONOSTEARATE; STEARYL ALCOHOL; .ALPHA.-TOCOPHEROL ACETATE

SOLVADERM Dermaxsol Dermal Defense Moisturizer SPF-30

ACTIVE INGREDIENTS:

Octocrylene 10.0%
Zinc Oxide 7.0%

PURPOSE

Sunscreen

USES:

Helps prevent sunburn.

WARNINGS:

For external use only.

Do not use

on damaged or broken skin.

When using this product

keep out of eyes. Rinse with water to remove.

Stop use and ask a doctor if

rash occurs.

Keep out of reach of children.

If product is swallowed, get medical help or contact a Poison Control Center right away.

DIRECTIONS:

Apply to all skin exposed to the sun.

*Apply liberally and evenly 15 minutes before sun exposure.

*Reapply at least every 2 hours.

*Use a water-resistant sunscreen if swimming or sweating.

*If pregnant or breast-feeding, ask a health care professional before use.

*For children under 6 months of age: Ask a doctor.

INACTIVE INGREDIENTS:

Aloe Barbadensis Leaf (Aloe Vera Gel) Juice, Aluminum Starch Octenyl succinate, Aqua (Deionized Water), Beeswax, Calendula Officinalis Extract, Camellia Sinensis (Green Tea) Extract, Chamomilla Matricaria Extract, Cetearyl Alcohol, Cyclopentasiloxane, Diisopropyl Adipate, Dimethicone, Dimethiconol, Ethylhexylglycerin, Glycerin, Glyceryl Laurate, Glyceryl Stearate, Hyaluronic Acid, C13-14 Isoparaffin, Laureth-7, Parfum (Fragrance)., PEG-100 Stearate, Phenoxyethanol, Polyacrylamide, Sorbitan Stearate, Stearyl Alcohol, Tocopheryl Acetate (Vitamin E).

OTHER INFORMATION:

Protect the product in this container from excessive heat and direct sun.